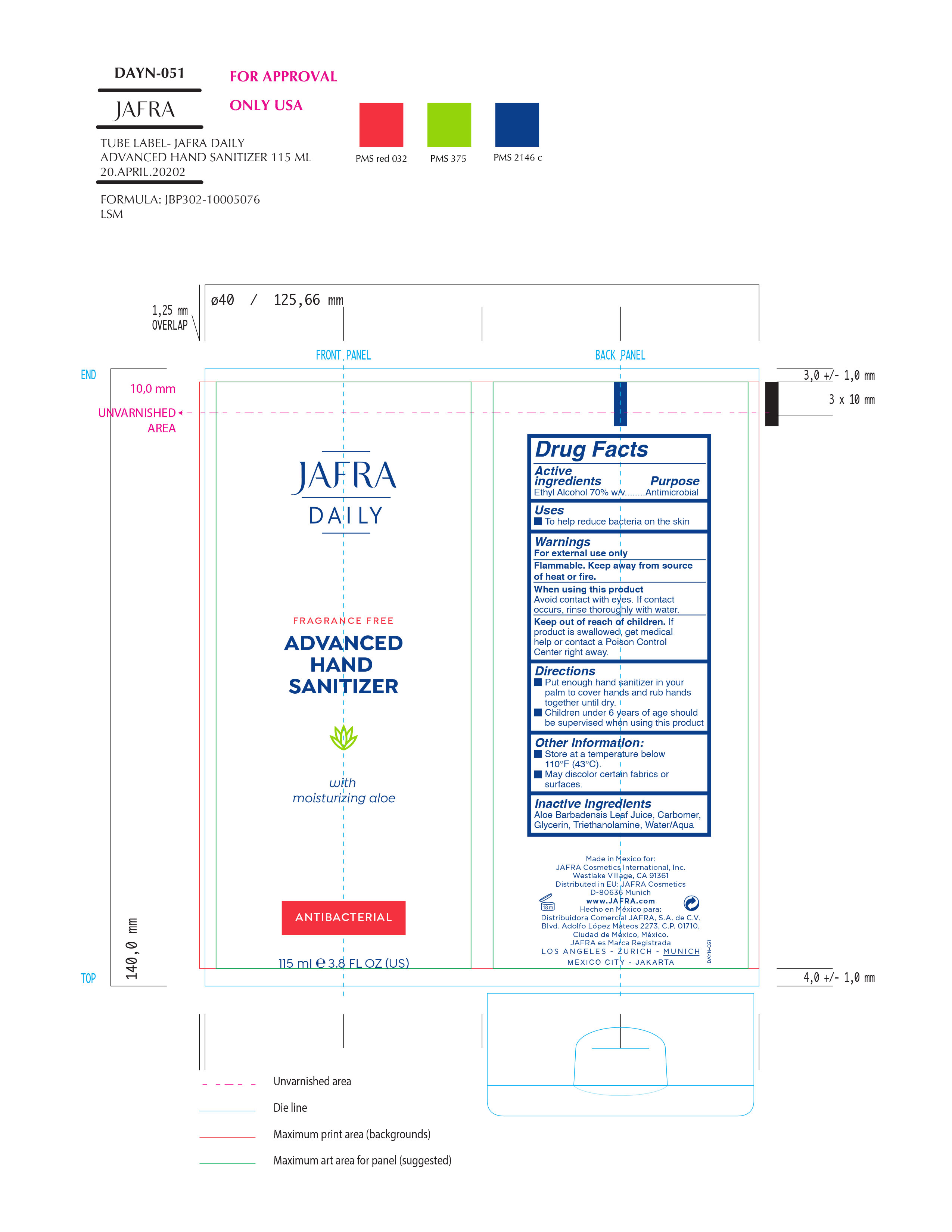 DRUG LABEL: Daily Advanced Hand Sanitizer
NDC: 68828-288 | Form: SOLUTION
Manufacturer: Jafra Cosmetics International Inc
Category: otc | Type: HUMAN OTC DRUG LABEL
Date: 20200501

ACTIVE INGREDIENTS: ALCOHOL 70 g/100 mL
INACTIVE INGREDIENTS: TROLAMINE; GLYCERIN; WATER; ALOE VERA LEAF; CARBOMER HOMOPOLYMER, UNSPECIFIED TYPE

Daily Advanced Hand Sanitizer

Active Ingredient(s)

Alcohol 80% v/v. Purpose: Antiseptic

Uses

- To help reduce bacteria on the skin

Keep out of reach of children. If swallowed, get medical help or contact a Poison Control Center right away.

When using this product

Avoid contact with eyes. If contact occurs rinse thoroughly with water.

WARNINGS

For external use only.

Flammable. Keep away from heat or flame

Directions

- Place enough product on hands to cover all surfaces. Rub hands together until dry.
- Supervise children under 6 years of age when using this product to avoid swallowing.

Inactive ingredients

Aloe Barbadensis Leaf juice, Carbomer, Glycerin, Triethanolamine, Water/Aqua

PACKAGE LABEL

Jafra Daily

Fragrance Free

Advanced Hand Sanitizer

with moisturizing aloe

Antibacterial

115 ml e 3.8 FL Oz (US)